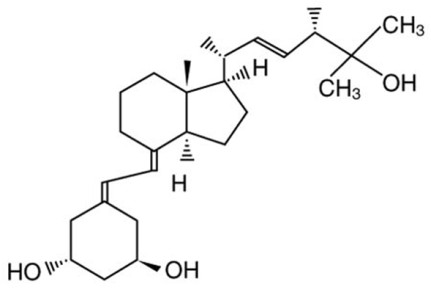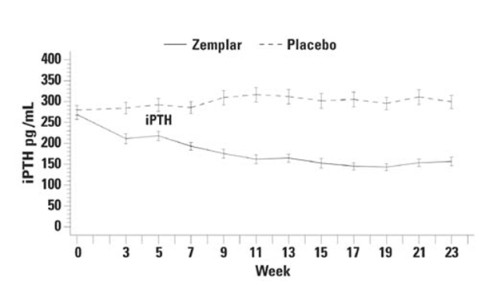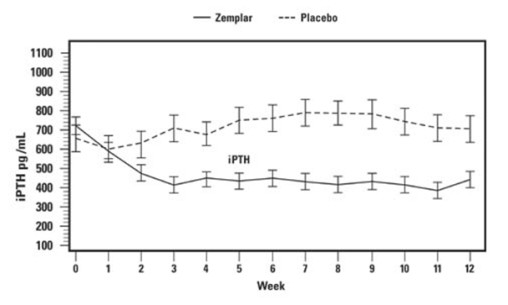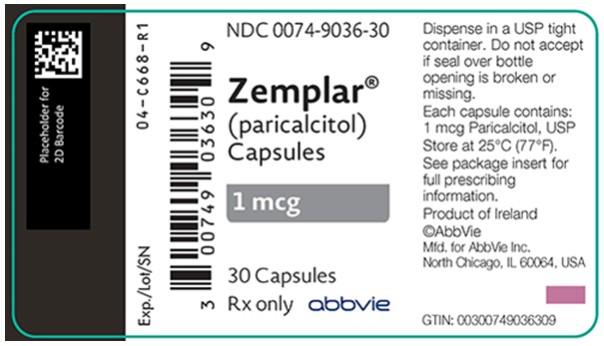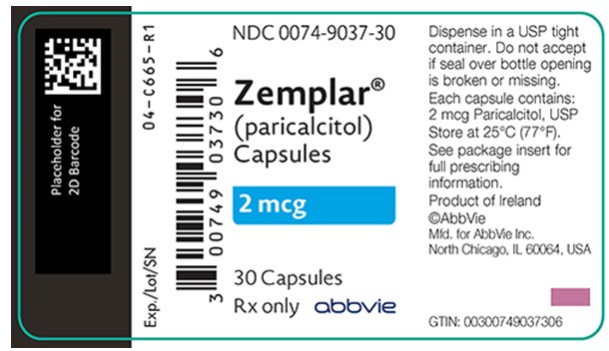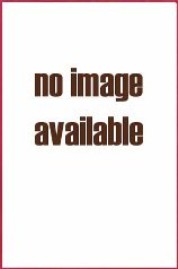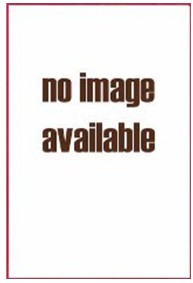 DRUG LABEL: Zemplar
NDC: 0074-4314 | Form: CAPSULE, LIQUID FILLED
Manufacturer: AbbVie Inc.
Category: prescription | Type: HUMAN PRESCRIPTION DRUG LABEL
Date: 20240807

ACTIVE INGREDIENTS: PARICALCITOL 2 ug/1 1
INACTIVE INGREDIENTS: GLYCERIN; TITANIUM DIOXIDE; WATER; FERRIC OXIDE RED; FERRIC OXIDE YELLOW; ALCOHOL; BUTYLATED HYDROXYTOLUENE; MEDIUM-CHAIN TRIGLYCERIDES; GELATIN, UNSPECIFIED

HIGHLIGHTS OF PRESCRIBING INFORMATION

These highlights do not include all the information needed to use ZEMPLAR safely and effectively.
See full prescribing information for ZEMPLAR.
ZEMPLAR (paricalcitol) capsules, for oral use
Initial U.S. Approval: 1998

1 INDICATIONS AND USAGE

ZEMPLAR is a vitamin D analog indicated in adults and pediatric patients 10 years and older for the prevention and treatment of secondary hyperparathyroidism associated with:

- Chronic kidney disease (CKD) Stages 3 and 4 (1.1).
- CKD Stage 5 in patients on hemodialysis or peritoneal dialysis (1.2).

2 DOSAGE AND ADMINISTRATION

Initial Dosage: CKD Stages 3 and 4 (2.1, 2.3)
Adult: Baseline iPTH ≤ 500 pg/mL | 1 mcg orally daily or 2 mcg three times a week*
Adult: Baseline iPTH > 500 pg/mL | 2 mcg orally daily or 4 mcg three times a week*
Pediatric: Ages 10 to 16 years | 1 mcg orally three times a week*
Dose Titration: CKD Stages 3 and 4 (2.1, 2.3)
Adult: iPTH same, increased or decreased by < 30% relative to baseline | Increase dose by 1 mcg daily or 2 mcg three times a week*
Adult: iPTH decreased by ≥ 30% and ≤ 60% relative to baseline | Maintain dose
Adult: iPTH decreased by > 60% or iPTH < 60 pg/mL relative to baseline | Decrease dose by 1 mcg daily or 2 mcg three times a week*
Pediatric: Ages 10 to 16 years | Increase each dose by 1 mcg three times a week every 4 weeks or decrease each dose by 1 mcg three times a week at any time based on iPTH, serum calcium and phosphorus levels.*
* Not more frequently than every other day when dosing three times a week.

Initial Dosage: CKD Stage 5 (2.2, 2.3)
Adult | Dose (micrograms) = baseline iPTH (pg/mL) divided by 80. Administer dose orally three times a week.*
Pediatric: Ages 10 to 16 years | Dose (micrograms) = baseline iPTH (pg/mL) divided by 120. Administer dose orally three times a week.*
Dose Titration: CKD Stage 5 (2.2, 2.3)
Adult | Dose in micrograms is based on most recent iPTH (pg/mL) divided by 80 with adjustments based on serum calcium and phosphorous levels. Dose three times a week.*
Pediatric: Ages 10 to 16 years | Increase each dose by 1 mcg three times a week every 4 weeks or decrease each dose by 2 mcg three times a week at any time based on iPTH, serum calcium and phosphorus levels.*
* Not more frequently than every other day.

- CKD Stage 5: To avoid hypercalcemia only treat patients after their baseline serum calcium has been reduced to 9.5 mg/dL or lower (2.2).

3 DOSAGE FORMS AND STRENGTHS

Capsules: 1 mcg and 2 mcg (3).

4 CONTRAINDICATIONS

- Evidence of hypercalcemia (4).
- Evidence of vitamin D toxicity (4).

5 WARNINGS AND PRECAUTIONS

- Hypercalcemia: Excessive administration of ZEMPLAR capsules can cause over suppression of PTH, hypercalcemia, hypercalciuria, hyperphosphatemia, and adynamic bone disease. Prescription-based doses of vitamin D and its derivatives should be withheld during ZEMPLAR treatment (5.1).
- Digitalis toxicity: Potentiated by hypercalcemia of any cause. Use caution when ZEMPLAR capsules are prescribed concomitantly with digitalis compounds (5.2).
- Laboratory tests: Monitor serum calcium, serum phosphorus, and serum or plasma iPTH during initial dosing or following any dose adjustment. ZEMPLAR capsules may increase serum creatinine and therefore decrease the estimated GFR (eGFR) (5.3).
- Aluminum overload and toxicity: Avoid excessive use of aluminum containing compounds (5.4).

6 ADVERSE REACTIONS

The most common adverse reactions (> 5% and more frequent than placebo) include diarrhea, nasopharyngitis, dizziness, vomiting, hypertension, hypersensitivity, nausea, and edema (6).

To report SUSPECTED ADVERSE REACTIONS, contact AbbVie Inc. at 1-800-633-9110 or FDA at 1-800-FDA-1088 or www.fda.gov/medwatch

7 DRUG INTERACTIONS

- Strong CYP3A inhibitors (e.g. ketoconazole) will increase the exposure of paricalcitol. Use with caution (7).
- Cholestyramine, Mineral Oil: Intestinal absorption of paricalcitol may be reduced if administered simultaneously with cholestyramine or mineral oil. Take ZEMPLAR Capsules at least 1 hour before or 4 to 6 hours after taking cholestyramine or mineral oil (7).

8 USE IN SPECIFIC POPULATIONS

Lactation: Breastfeeding not recommended (8.2).

FULL PRESCRIBING INFORMATION

1 INDICATIONS AND USAGE

1.1 Chronic Kidney Disease Stages 3 and 4

ZEMPLAR capsules are indicated in adults and pediatric patients 10 years of age and older for the prevention and treatment of secondary hyperparathyroidism associated with Chronic Kidney Disease (CKD) Stages 3 and 4.

1.2 Chronic Kidney Disease Stage 5

ZEMPLAR capsules are indicated in adults and pediatric patients 10 years of age and older for the prevention and treatment of secondary hyperparathyroidism associated with CKD Stage 5 in patients on hemodialysis (HD) or peritoneal dialysis (PD).

2 DOSAGE AND ADMINISTRATION

2.1 Chronic Kidney Disease Stages 3 and 4 in Adults

Administer ZEMPLAR capsules orally once daily or three times a week [see Clinical Studies (14.1)]. When dosing three times weekly, do not administer more frequently than every other day.

Initial Dose

Table 1. Recommended ZEMPLAR Starting Dose Based upon Baseline iPTH Level
Baseline iPTH Level | Daily Dose | Three Times a Week Dose*
Less than or equal to 500 pg/mL | 1 mcg | 2 mcg
More than 500 pg/mL | 2 mcg | 4 mcg
* To be administered not more often than every other day

Dose Titration

Table 2. Recommended ZEMPLAR Dose Titration Base upon iPTH Level
 |  | Dose Adjustment at 2 to 4 Week Intervals
iPTH Level Relative to Baseline | ZEMPLAR Capsule Dose | Daily Dosage | Three Times a Week Dosage*
The same, increased or decreased by less than 30% | Increase dose by | 1 mcg | 2 mcg
Decreased by more than or equal to 30% and less than or equal to 60% | Maintain dose | - | -
Decreased by more than 60% or iPTH less than 60 pg/mL | Decrease dose by | 1 mcg | 2 mcg
* To be administered not more often than every other day

If a patient is taking the lowest dose, 1 mcg, on the daily regimen and a dose reduction is needed, the dose can be decreased to 1 mcg three times a week. If a further dose reduction is required, the drug should be withheld as needed and restarted at a lower dosing frequency.

2.2 Chronic Kidney Disease Stage 5 in Adults

Initial Dose

Administer the dose of ZEMPLAR capsules orally three times a week, no more frequently than every other day based upon the following formula:

Dose (micrograms) = baseline iPTH (pg/mL) divided by 80

Treat patients only after their baseline serum calcium has been adjusted to 9.5 mg/dL or lower to minimize the risk of hypercalcemia [see Clinical Pharmacology (12.2) and Clinical Studies (14.2)].

Dose Titration

Individualize the dose of ZEMPLAR based on iPTH, serum calcium and phosphorus levels. Titrate ZEMPLAR dose based on the following formula:

Dose (micrograms) = most recent iPTH level (pg/ml) divided by 80

If serum calcium is elevated, the dose should be decreased by 2 to 4 micrograms.

As iPTH approaches the target range, small, individualized dose adjustments may be necessary in order to achieve a stable iPTH. In situations where monitoring of iPTH, Ca or P occurs less frequently than once per week, a more modest initial and dose titration ratio (e.g., iPTH divided by 100) may be warranted.

2.3 Pediatric Patients (Ages 10 to 16 Years)

CKD Stages 3 and 4

Initial Dose

Administer ZEMPLAR 1 mcg capsule orally three times a week, no more frequently than every other day.

Dose Titration

Individualize and titrate ZEMPLAR dose based on iPTH, serum calcium and phosphorus levels to maintain an iPTH level within target range.

Every 4 weeks, each administered ZEMPLAR dose may be increased in 1 mcg increments, maintaining the three times per week regimen (e.g., increase from 1 mcg three times per week to 2 mcg three times per week). At any time, each administered dose may be decreased by 1 mcg. ZEMPLAR may be stopped if the patient requires reduction while receiving 1 mcg three times per week, resuming when appropriate.

CKD Stage 5

Initial Dose

Administer the dose of ZEMPLAR capsules orally three times a week, no more frequently than every other day based upon the following formula:

Dose* (micrograms) = baseline iPTH (pg/mL) divided by 120
* Round down to the nearest whole number

Dose Titration

Subsequent dosing should be individualized and based on iPTH, serum calcium and phosphorus levels to maintain an iPTH level within target range.

Every 4 weeks, each administered ZEMPLAR dose may be increased in 1 mcg increments, maintaining the three times per week regimen (e.g., increase from 1 mcg three times per week to 2 mcg three times per week). At any time, each administered dose may be decreased by 2 mcg. ZEMPLAR may be stopped if the patient requires reduction while receiving 2 mcg three times per week or 1 mcg three times per week, resuming when appropriate.

2.4 Monitoring

Monitor serum calcium and phosphorus levels closely after initiation of ZEMPLAR, during dose titration periods and during co-administration with strong CYP3A inhibitors [see Warnings and Precautions (5.3), Drug Interactions (7), and Clinical Pharmacology (12.3)].

If hypercalcemia is observed, the dose of ZEMPLAR should be reduced or withheld until these parameters are normalized.

2.5 Administration

ZEMPLAR capsules may be taken without regard to food.

3 DOSAGE FORMS AND STRENGTHS

ZEMPLAR capsules are available as 1 mcg and 2 mcg soft gelatin capsules.

- 1 mcg: oval, gray capsule imprinted with “ZA”
- 1 mcg: oval, gray capsule imprinted with the “a” logo and “ZA”
- 2 mcg: oval, orange-brown capsule imprinted with “ZF”
- 2 mcg: oval, orange-brown capsule imprinted with the “a” logo and “ZF”

4 CONTRAINDICATIONS

ZEMPLAR capsules should not be given to patients with evidence of

- hypercalcemia or
- vitamin D toxicity [see Warnings and Precautions (5.1)].

5 WARNINGS AND PRECAUTIONS

Excessive administration of vitamin D compounds, including ZEMPLAR capsules, can cause over suppression of PTH, hypercalcemia, hypercalciuria, hyperphosphatemia, and adynamic bone disease.

5.1 Hypercalcemia

Progressive hypercalcemia due to overdosage of vitamin D and its metabolites may be so severe as to require emergency attention [see Overdosage (10)]. Acute hypercalcemia may exacerbate tendencies for cardiac arrhythmias and seizures and may potentiate the action of digitalis. Chronic hypercalcemia can lead to generalized vascular calcification and other soft-tissue calcification. Concomitant administration of high doses of calcium-containing preparations or thiazide diuretics with ZEMPLAR may increase the risk of hypercalcemia. High intake of calcium and phosphate concomitant with vitamin D compounds may lead to serum abnormalities requiring more frequent patient monitoring and individualized dose titration. Patients also should be informed about the symptoms of elevated calcium, which include feeling tired, difficulty thinking clearly, loss of appetite, nausea, vomiting, constipation, increased thirst, increased urination and weight loss.

Prescription-based doses of vitamin D and its derivatives should be withheld during ZEMPLAR treatment to avoid hypercalcemia.

5.2 Digitalis Toxicity

Digitalis toxicity is potentiated by hypercalcemia of any cause. Use caution when ZEMPLAR capsules are prescribed concomitantly with digitalis compounds.

5.3 Laboratory Tests

During the initial dosing or following any dose adjustment of medication, serum calcium, serum phosphorus, and serum or plasma iPTH should be monitored at least every two weeks for 3 months, then monthly for 3 months, and every 3 months thereafter.

In pre-dialysis patients, ZEMPLAR capsules may increase serum creatinine and therefore decrease the estimated GFR (eGFR). Similar effects have also been seen with calcitriol.

5.4 Aluminum Overload and Toxicity

Aluminum-containing preparations (e.g., antacids, phosphate binders) should not be administered chronically with ZEMPLAR, as increased blood levels of aluminum and aluminum bone toxicity may occur.

6 ADVERSE REACTIONS

Because clinical studies are conducted under widely varying conditions, adverse reaction rates observed in the clinical studies of a drug cannot be directly compared to rates in the clinical studies of another drug and may not reflect the rates observed in practice.

6.1 Clinical Trials Experience

CKD Stages 3 and 4

Adults

The safety of ZEMPLAR capsules has been evaluated in three 24-week (approximately six-month), double-blind, placebo-controlled, multicenter clinical studies involving 220 CKD Stages 3 and 4 patients. Six percent (6%) of ZEMPLAR capsules treated patients and 4% of placebo treated patients discontinued from clinical studies due to an adverse event. Adverse events occurring in the ZEMPLAR capsules group at a frequency of 2% or greater and more frequently than in the placebo group are presented in Table 3:

Table 3. Adverse Reactions by Body System Occurring in ≥ 2% of Subjects in the ZEMPLAR-Treated Group of Three, Double-Blind, Placebo-Controlled CKD Stages 3 and 4 Studies
 | Number (%) of Subjects
Adverse Eventa | ZEMPLAR Capsules (n = 107) |  | Placebo (n = 113)
Overall | 88 | (82%) | 86 | (76%)
Ear and Labyrinth Disorders
Vertigo | 5 | (5%) | 0 | (0%)
Gastrointestinal Disorders
Abdominal Discomfort | 4 | (4%) | 1 | (1%)
Constipation | 4 | (4%) | 4 | (4%)
Diarrhea | 7 | (7%) | 5 | (4%)
Nausea | 6 | (6%) | 4 | (4%)
Vomiting | 5 | (5%) | 5 | (4%)
General Disorders and Administration Site Conditions
Chest Pain | 3 | (3%) | 1 | (1%)
Edema | 6 | (6%) | 5 | (4%)
Pain | 4 | (4%) | 4 | (4%)
Immune System Disorders
Hypersensitivity | 6 | (6%) | 2 | (2%)
Infections and Infestations
Fungal Infection | 3 | (3%) | 0 | (0%)
Gastroenteritis | 3 | (3%) | 3 | (3%)
Infection | 3 | (3%) | 3 | (3%)
Sinusitis | 3 | (3%) | 1 | (1%)
Urinary Tract Infection | 3 | (3%) | 1 | (1%)
Viral Infection | 8 | (7%) | 8 | (7%)
Metabolism and Nutrition Disorders
Dehydration | 3 | (3%) | 1 | (1%)
Musculoskeletal and Connective Tissue Disorders
Arthritis | 5 | (5%) | 0 | (0%)
Back Pain | 3 | (3%) | 1 | (1%)
Muscle Spasms | 3 | (3%) | 0 | (0%)
Nervous System Disorders
Dizziness | 5 | (5%) | 5 | (4%)
Headache | 5 | (5%) | 5 | (4%)
Syncope | 3 | (3%) | 1 | (1%)
Psychiatric Disorders
Depression | 3 | (3%) | 0 | (0%)
Respiratory, Thoracic and Mediastinal Disorders
Cough | 3 | (3%) | 2 | (2%)
Oropharyngeal Pain | 4 | (4%) | 0 | (0%)
Skin and Subcutaneous Tissue Disorders
Pruritus | 3 | (3%) | 3 | (3%)
Rash | 4 | (4%) | 1 | (1%)
Skin Ulcer | 3 | (3%) | 0 | (0%)
Vascular Disorders
Hypertension | 7 | (7%) | 4 | (4%)
Hypotension | 5 | (5%) | 3 | (3%)
a. Includes only events more common in the ZEMPLAR treatment group.

Additional Adverse Reactions

The following additional adverse reactions occurred in <2% of the ZEMPLAR-treated patients in the above double-blind, placebo-controlled clinical trial.

Gastrointestinal Disorders: Dry mouth

Investigations: Hepatic enzyme abnormal

Nervous System Disorders: Dysgeusia

Skin and Subcutaneous Tissue Disorders: Urticaria

Pediatric patients 10 to 16 years of age

The safety of ZEMPLAR capsules has been evaluated in one multicenter clinical study involving CKD Stages 3 and 4 patients ages 10 to 16 years. A 12-week double-blind, placebo-controlled phase was followed by an open-label phase during which all patients received ZEMPLAR capsules.

During the 12-week blinded phase, a total of 18 patients received ZEMPLAR capsules and 18 patients received placebo. Adverse events occurring more frequently in the ZEMPLAR capsules group than in the placebo group are presented in Table 4.

Table 4. Adverse Reactions by Body System Occurring in the Double-Blind, Placebo-Controlled, CKD Stages 3 and 4 Study in Patients Ages 10 to 16 Years
 | Number (%) of Subjects
Adverse Eventa | ZEMPLAR Capsules (n = 18) |  | Placebo (n = 18)
Overall | 7 | (39%) | 16 | (89%)
Gastrointestinal Disorders
Nausea | 1 | (6%) | 0 | (0%)
Infections and Infestations
Conjunctivitis | 1 | (6%) | 0 | (0%)
Rhinitis | 3 | (17%) | 0 | (0%)
Renal and Urinary Disorders
Micturition Urgency | 1 | (6%) | 0 | (0%)
Respiratory, Thoracic and Mediastinal Disorders
Asthma | 1 | (6%) | 0 | (0%)
a. Includes only events more common in the ZEMPLAR treatment group.

Additional Adverse Reactions

The following adverse reactions have occurred in ZEMPLAR-treated patients:

Gastrointestinal Disorders: Abdominal pain, constipation, vomiting

Metabolism and Nutrition Disorders: Hypercalcemia and hyperphosphatemia

Nervous System Disorders: Headache

CKD Stage 5

Adults

The safety of ZEMPLAR capsules has been evaluated in one 12-week, double-blind, placebo-controlled, multicenter clinical study involving 88 CKD Stage 5 patients. Sixty-one patients received ZEMPLAR capsules and 27 patients received placebo.

The proportion of patients who terminated prematurely from the study due to adverse events was 7% for ZEMPLAR capsules treated patients and 7% for placebo patients.

Adverse events occurring in the ZEMPLAR capsules group at a frequency of 2% or greater and more frequently than in the placebo group are as follows:

Table 5. Adverse Reactions by Body System Occurring in ≥ 2% of Subjects in the ZEMPLAR-Treated Group, Double-Blind, Placebo-Controlled CKD Stage 5 Study
 | Number (%) of Subjects
Adverse Eventsa | ZEMPLAR Capsules (n=61) |  | Placebo (n = 27)
Overall | 43 | (70%) | 19 | (70%)
Gastrointestinal Disorders
Constipation | 3 | (5%) | 0 | (0%)
Diarrhea | 7 | (11%) | 3 | (11%)
Vomiting | 4 | (7%) | 0 | (0%)
General Disorders and Administration Site Conditions
Fatigue | 2 | (3%) | 0 | (0%)
Edema Peripheral | 2 | (3%) | 0 | (0%)
Infections and Infestations
Nasopharyngitis | 5 | (8%) | 2 | (7%)
Peritonitis | 3 | (5%) | 0 | (0%)
Sinusitis | 2 | (3%) | 0 | (0%)
Urinary Tract Infection | 2 | (3%) | 0 | (0%)
Metabolism and Nutrition Disorders
Fluid Overload | 3 | (5%) | 0 | (0%)
Hypoglycemia | 2 | (3%) | 0 | (0%)
Nervous System Disorders
Dizziness | 4 | (7%) | 0 | (0%)
Headache | 2 | (3%) | 0 | (0%)
Psychiatric Disorders
Anxiety | 2 | (3%) | 0 | (0%)
Insomnia | 3 | (5%) | 0 | (0%)
Renal and Urinary Disorders
Renal Failure Chronic | 2 | (3%) | 0 | (0%)
a. Includes only events more common in the ZEMPLAR treatment group.

Additional Adverse Reactions

The following adverse reactions occurred in <2% of the ZEMPLAR-treated patients in the above double-blind, placebo-controlled clinical trial.

Gastrointestinal Disorders: Gastroesophageal reflux disease

Metabolism and Nutrition Disorders: Decreased appetite, hypercalcemia, hypocalcemia

Reproductive System and Breast Disorders: Breast tenderness

Skin and Subcutaneous Tissue Disorders: Acne

Pediatric patients 10 to 16 years of age

The safety of ZEMPLAR capsules has been evaluated in one 12-week, open-label, single-arm, multicenter clinical studies involving 13 CKD Stage 5 patients ages 10 to 16 years of age receiving peritoneal dialysis or hemodialysis.

The following adverse reactions were reported:

Gastrointestinal Disorders: Abdominal pain, diarrhea, nausea, vomiting

Metabolism and Nutrition Disorders: Hypercalcemia, hyperphosphatemia

Three of 13 patients (23%) had hypercalcemia defined as at least 2 consecutive serum calcium values >10.2 mg/dL (2.55 mmol/L).

6.2 Postmarketing Experience

The following adverse reactions have been identified during post-approval use of ZEMPLAR capsules. Because these reactions are reported voluntarily from a population of uncertain size, it is not always possible to reliably estimate their frequency or establish a causal relationship to drug exposure.

Immune System Disorders: Angioedema (including laryngeal edema)

Investigations: Blood creatinine increased

7 DRUG INTERACTIONS

Table 6 shows the clinically significant drug interactions with ZEMPLAR capsules.

Table 6: Clinically Significant Drug Interactions with Paricalcitol
CYP3A Inhibitors
Clinical Impact | Paricalcitol is partially metabolized by CYP3A. Hence, exposure of paricalcitol will increase upon coadministration with strong CYP3A inhibitors such as but not limited to: boceprevir, clarithromycin, conivaptan, grapefruit juice, indinavir, itraconazole, ketoconazole, lopinavir/ritonavir, mibefradil, nefazodone, nelfinavir, posaconazole, ritonavir, saquinavir, telaprevir, telithromycin, voriconazole.
Intervention | Dose adjustment of ZEMPLAR capsules may be necessary. Monitor closely for iPTH and serum calcium concentrations, if a patient initiates or discontinues therapy with a strong CYP3A4 inhibitor.
Cholestyramine
Clinical Impact | Drugs that impair intestinal absorption of fat-soluble vitamins, such as cholestyramine, may interfere with the absorption of paricalcitol.
Intervention | Recommend to take ZEMPLAR capsules at least 1 hour before or 4 to 6 hours after taking cholestyramine (or at as great an interval as possible) to avoid impeding absorption of paricalcitol.
Mineral Oil
Clinical Impact | Mineral oil or other substances that may affect absorption of fat may influence the absorption of paricalcitol.
Intervention | Recommend to take ZEMPLAR capsules at least 1 hour before or 4 to 6 hours after taking mineral oil (or at as great an interval as possible) to avoid affecting absorption of paricalcitol.

8 USE IN SPECIFIC POPULATIONS

8.1 Pregnancy

Risk Summary

Limited data with ZEMPLAR capsules in pregnant women are insufficient to inform a drug-associated risk for major birth defects and miscarriage. There are risks to the mother and fetus associated with chronic kidney disease in pregnancy [see Clinical Considerations].

In animal reproduction studies, slightly increased embryofetal loss was observed in pregnant rats and rabbits administered paricalcitol intravenously during the period of organogenesis at doses 2 and 0.5 times, respectively, the maximum recommended human dose (MRHD). Adverse reproductive outcomes were observed at doses that caused maternal toxicity [see Data].

The estimated background risk of major birth defects and miscarriage for the indicated population is unknown. All pregnancies have a background risk of birth defect, loss, or other adverse outcomes. In the U.S. general population, the estimated background risk of major birth defects and miscarriage in clinically recognized pregnancies is 2-4% and 15-20%, respectively.

Clinical Considerations

Disease-associated maternal and/or embryo/fetal risk

Chronic kidney disease in pregnancy increases the maternal risk for hypertension, spontaneous abortion, preterm labor, and preeclampsia. Chronic kidney disease increases the fetal risk for intrauterine growth restriction (IUGR), prematurity, polyhydramnios, still birth, and low birth weight.

Data

Animal Data

Pregnant rats and rabbits were treated with paricalcitol by once-daily intravenous (IV) injection during the period of organogenesis (in rats, from gestation day (GD) 6 to 17; in rabbits, from GD 6 to 18). Rats were dosed at 0, 0.3, 1.0 or 3.0 mcg/kg/day and rabbits at 0, 0.03, 0.1 or 0.3 mcg/kg/day, representing up to 2 or 0.5 times, respectively, the maximum recommended human dose (MRHD) of 0.24 mcg/kg, based on body surface area (mcg/m^2). Slightly decreased fetal viability was observed in both studies at the highest doses representing 2 and 0.5 times, respectively, the MRHD in the presence of maternal toxicity (decreased body weight and food consumption). Pregnant rats were administered paricalcitol by IV injection three times per week at doses of 0, 0.3, 3.0 or 20.0 mcg/kg/day throughout gestation, parturition and lactation (GD 6 to lactation day (LD) 20) representing exposures up to 13 times the MHRD. A small increase in stillbirths and pup deaths from parturition to LD 4 were observed at the high dose when compared to the control group (9.2% versus 3.3% in controls) at 13 times the MRHD, which occurred at a maternally toxic dose known to cause hypercalcemia in rats. Surviving pups were not adversely affected; body weight gains, developmental landmarks, reflex ontogeny, learning indices, and locomotor activity were all within normal parameters. F1 reproductive capacity was unaffected.

8.2 Lactation

Risk Summary

There is no information available on the presence of paricalcitol in human milk, the effects of the drug on the breastfed infant or the effects of the drug on milk production. Studies in rats have shown that paricalcitol and/or its metabolites are present in the milk of lactating rats; however, due to specifies-specific differences in lactation physiology, animal data may not reliably predict drug levels in human milk [see Data]. Because of the potential for serious adverse reactions, including hypercalcemia in a breastfed infant, advise patients that breastfeeding is not recommended during treatment with ZEMPLAR.

Data

Following a single oral administration of 20 mcg/kg of radioactive [^3H] paricalcitol to lactating rats, the concentrations of total radioactivity was determined. Lower levels of total radioactivity were present in the milk compared to that in the plasma of the dams indicating that low levels of [^3H] paricalcitol and/or its metabolites are secreted into milk. Exposure of the pups to [^3H] paricalcitol through milk was confirmed by the presence of radioactive material in the pups’ stomachs.

8.4 Pediatric Use

The safety and effectiveness of ZEMPLAR capsules have been established in pediatric patients 10 to 16 years of age for the prevention and treatment of secondary hyperparathyroidism associated with Stage 3, 4, and 5 CKD.

Use of ZEMPLAR capsules in this age group is supported by evidence from adequate and well controlled studies in adults with CKD, a 12-week double-blind placebo-controlled randomized multicenter study in 36 pediatric patients 10 to 16 years of age with CKD Stages 3 and 4, and safety data from a 12-week open-label single-arm multicenter study in 13 pediatric patients 10 to 16 years of age with CKD Stage 5 receiving peritoneal dialysis or hemodialysis. The pharmacokinetics of paricalcitol in Stage 5 CKD pediatric patients appear to be similar to those observed in Stage 3 and 4 pediatric patients [see Clinical Pharmacology (12.3) and Clinical Studies (14.1)].

Adverse reactions reported in these pediatric studies are consistent with the known safety profile of ZEMPLAR capsules and with what has been reported in adult clinical studies [see Adverse Reactions (6.1)].

Safety and effectiveness of ZEMPLAR capsules in pediatric patients under the age of 10 years have not been established.

8.5 Geriatric Use

Of the total number (n = 220) of CKD Stages 3 and 4 patients in clinical studies of ZEMPLAR capsules, 49% were age 65 and over, while 17% were age 75 and over. Of the total number (n = 88) of CKD Stage 5 patients in the pivotal study of ZEMPLAR capsules, 28% were age 65 and over, while 6% were age 75 and over. No overall differences in safety and effectiveness were observed between these patients and younger patients, and other reported clinical experience has not identified differences in responses between the elderly and younger patients, but greater sensitivity of some older individuals cannot be ruled out.

10 OVERDOSAGE

Excessive administration of ZEMPLAR capsules can cause hypercalcemia, hypercalciuria, and hyperphosphatemia, and over suppression of PTH [see Warnings and Precautions (5.1)].

Treatment of Overdosage

The treatment of acute overdosage of ZEMPLAR capsules should consist of general supportive measures. If drug ingestion is discovered within a relatively short time, induction of emesis or gastric lavage may be of benefit in preventing further absorption. If the drug has passed through the stomach, the administration of mineral oil may promote its fecal elimination. Serial serum electrolyte determinations (especially calcium), rate of urinary calcium excretion, and assessment of electrocardiographic abnormalities due to hypercalcemia should be obtained. Such monitoring is critical in patients receiving digitalis. Discontinuation of supplemental calcium and institution of a low-calcium diet are also indicated in accidental overdosage. Due to the relatively short duration of the pharmacological action of paricalcitol, further measures are probably unnecessary. If persistent and markedly elevated serum calcium levels occur, there are a variety of therapeutic alternatives that may be considered depending on the patient's underlying condition. These include the use of drugs such as phosphates and corticosteroids, as well as measures to induce an appropriate forced diuresis.

Paricalcitol is not significantly removed by dialysis.

11 DESCRIPTION

Paricalcitol, USP, the active ingredient in ZEMPLAR capsules, is a synthetically manufactured, metabolically active vitamin D analog of calcitriol with modifications to the side chain (D2) and the A (19-nor) ring. ZEMPLAR is available as soft gelatin capsules for oral administration containing 1 microgram or 2 micrograms of paricalcitol. Each capsule also contains medium chain triglycerides, alcohol, and butylated hydroxytoluene. The medium chain triglycerides are fractionated from coconut oil or palm kernel oil. The capsule shell is composed of gelatin, glycerin, titanium dioxide, iron oxide red (2 microgram capsules only), iron oxide yellow (2 microgram capsules only), iron oxide black (1 microgram capsules only), and water.

Paricalcitol is a white, crystalline powder with the empirical formula of C27H44O3, which corresponds to a molecular weight of 416.64. Paricalcitol is chemically designated as 19-nor-1α,3β,25-trihydroxy-9,10-secoergosta-5(Z),7(E),22(E)-triene and has the following structural formula:

12 CLINICAL PHARMACOLOGY

Secondary hyperparathyroidism is characterized by an elevation in parathyroid hormone (PTH) associated with inadequate levels of active vitamin D hormone. The source of vitamin D in the body is from synthesis in the skin as vitamin D3 and from dietary intake as either vitamin D2 or D3. Both vitamin D2 and D3 require two sequential hydroxylations in the liver and the kidney to bind to and to activate the vitamin D receptor (VDR). The endogenous VDR activator, calcitriol [1,25(OH)2D3], is a hormone that binds to VDRs that are present in the parathyroid gland, intestine, kidney, and bone to maintain parathyroid function and calcium and phosphorus homeostasis, and to VDRs found in many other tissues, including prostate, endothelium and immune cells. VDR activation is essential for the proper formation and maintenance of normal bone. In the diseased kidney, the activation of vitamin D is diminished, resulting in a rise of PTH, subsequently leading to secondary hyperparathyroidism and disturbances in the calcium and phosphorus homeostasis. Decreased levels of 1,25(OH)2D3 have been observed in early stages of chronic kidney disease. The decreased levels of 1,25(OH)2D3 and resultant elevated PTH levels, both of which often precede abnormalities in serum calcium and phosphorus, affect bone turnover rate and may result in renal osteodystrophy.

12.1 Mechanism of Action

Paricalcitol is a synthetic, biologically active vitamin D2 analog of calcitriol. Preclinical and in vitro studies have demonstrated that paricalcitol's biological actions are mediated through binding of the VDR, which results in the selective activation of vitamin D responsive pathways. Vitamin D and paricalcitol have been shown to reduce parathyroid hormone levels by inhibiting PTH synthesis and secretion.

12.2 Pharmacodynamics

Paricalcitol decreases serum intact parathyroid hormone (iPTH) and increases serum calcium and serum phosphorous in both HD and PD patients. This observed relationship was quantified using a mathematical model for HD and PD patient populations separately. Computer-based simulations of 100 trials in HD or PD patients (N = 100) using these relationships predict slightly lower efficacy (at least two consecutive ≥ 30% reductions from baseline iPTH) with lower hypercalcemia rates (at least two consecutive serum calcium ≥ 10.5 mg/dL) for lower iPTH-based dosing regimens. Further lowering of hypercalcemia rates was predicted if the treatment with paricalcitol is initiated in patients with lower serum calcium levels at screening.

Based on these simulations, a dosing regimen of iPTH/80 with a screening serum calcium ≤ 9.5 mg/dL, approximately 76.5% (95% CI: 75.6% – 77.3%) of HD patients are predicted to achieve at least two consecutive weekly ≥ 30% reductions from baseline iPTH over a duration of 12 weeks. The predicted incidence of hypercalcemia is 0.8% (95% CI: 0.7% – 1.0%). In PD patients, with this dosing regimen, approximately 83.3% (95% CI: 82.6% – 84.0%) of patients are predicted to achieve at least two consecutive weekly ≥ 30% reductions from baseline iPTH. The predicted incidence of hypercalcemia is 12.4% (95% CI: 11.7% - 13.0%) [see Clinical Studies (14.2) and Dosage and Administration (2.2)].

12.3 Pharmacokinetics

Absorption

The mean absolute bioavailability of ZEMPLAR capsules under low-fat fed condition ranged from 72% to 86% in healthy adult volunteers, CKD Stage 5 patients on HD, and CKD Stage 5 patients on PD. A food effect study in healthy adult volunteers indicated that the Cmax and AUC0-∞ were unchanged when paricalcitol was administered with a high fat meal compared to fasting. Food delayed Tmax by about 2 hours. The AUC0-∞ of paricalcitol increased proportionally over the dose range of 0.06 to 0.48 mcg/kg in healthy adult volunteers.

Distribution

Paricalcitol is extensively bound to plasma proteins (≥ 99.8%). The mean apparent volume of distribution following a 0.24 mcg/kg dose of paricalcitol in healthy adult volunteers was 34 L. The mean apparent volume of distribution following a 4 mcg dose of paricalcitol in CKD Stage 3 and a 3 mcg dose in CKD Stage 4 patients is between 44 and 46 L.

Metabolism

After oral administration of a 0.48 mcg/kg dose of ^3H-paricalcitol, parent drug was extensively metabolized, with only about 2% of the dose eliminated unchanged in the feces, and no parent drug was found in the urine. Several metabolites were detected in both the urine and feces. Most of the systemic exposure was from the parent drug. Two minor metabolites, relative to paricalcitol, were detected in human plasma. One metabolite was identified as 24(R)-hydroxy paricalcitol, while the other metabolite was unidentified. The 24(R)-hydroxy paricalcitol is less active than paricalcitol in an in vivo rat model of PTH suppression.

In vitro data suggest that paricalcitol is metabolized by multiple hepatic and non-hepatic enzymes, including mitochondrial CYP24, as well as CYP3A4 and UGT1A4. The identified metabolites include the product of 24(R)-hydroxylation, 24,26- and 24,28-dihydroxylation and direct glucuronidation.

Elimination

Paricalcitol is eliminated primarily via hepatobiliary excretion; approximately 70% of the radiolabeled dose is recovered in the feces and 18% is recovered in the urine. While the mean elimination half-life of paricalcitol is 4 to 6 hours in healthy adult volunteers, the mean elimination half-life of paricalcitol in CKD Stages 3, 4, and 5 (on HD and PD) patients ranged from 14 to 20 hours.

Table 7. Paricalcitol Capsule Pharmacokinetic Parameters (mean ± SD) in CKD Stages 3, 4, and 5 Adult Patients
Pharmacokinetic Parameters (units) | CKD Stage 3 n = 15* | CKD Stage 4 n = 14* | CKD Stage 5 HD** n = 14 | CKD Stage 5 PD** n = 8
Cmax (ng/mL) | 0.11 ± 0.04 | 0.06 ± 0.01 | 0.575 ± 0.17 | 0.413 ± 0.06
AUC0-∞ (ng•h/mL) | 2.42 ± 0.61 | 2.13 ± 0.73 | 11.67 ± 3.23 | 13.41 ± 5.48
CL/F (L/h) | 1.77 ± 0.50 | 1.52 ± 0.36 | 1.82 ± 0.75 | 1.76 ± 0.77
V/F (L) | 43.7 ± 14.4 | 46.4 ± 12.4 | 38 ± 16.4 | 48.7 ± 15.6
t1/2 | 16.8 ± 2.65 | 19.7 ± 7.2 | 13.9 ± 5.1 | 17.7 ± 9.6
HD: hemodialysis; PD: peritoneal dialysis.
* Four mcg paricalcitol capsules were given to CKD Stage 3 patients; three mcg paricalcitol capsules were given to CKD Stage 4 patients.
** CKD Stage 5 HD and PD patients received a 0.24 mcg/kg dose of paricalcitol as capsules.

Specific Populations

Geriatric

The pharmacokinetics of paricalcitol has not been investigated in geriatric patients greater than 65 years [see Use in Specific Populations (8.5)].

Pediatric

Paricalcitol Cmax, AUC, and t1/2 values were similar between Stage 3 and Stage 4 CKD pediatric patients 10 to 16 years of age. Population pharmacokinetic analysis shows that the pharmacokinetics of paricalcitol in Stage 5 CKD pediatric patients appear to be similar to those observed in Stage 3 and Stage 4 pediatric patients.

Table 8. Paricalcitol Capsules Pharmacokinetic Parameters (mean ± SD) in CKD Stages 3 and 4 Patients 10 to 16 Years of Age
Pharmacokinetic Parameter (units) | CKD Stage 3 n = 6 | CKD Stage 4 N = 5
Cmax (ng/mL) | 0.12 ± 0.06 | 0.13 ± 0.05
AUC∞ (ng•h/mL) | 2.63 ± 0.76 | 3.2 ± 0.99
CL/F (L/h) | 1.23 ± 0.38 | 1.02 ± 0.35
V/F (L) | 27.78 ± 18.60 | 24.36 ± 5.92
t1/2 (h) | 15.0 ± 6.1 | 17.5 ± 5.9
* Three 1 mcg paricalcitol capsules were given to CKD Stage 3 or 4 patients.

Gender

The pharmacokinetics of paricalcitol following single doses over the 0.06 to 0.48 mcg/kg dose range was gender independent.

Hepatic Impairment

The disposition of paricalcitol (0.24 mcg/kg) was compared in patients with mild (n = 5) and moderate (n = 5) hepatic impairment (as indicated by the Child-Pugh method) and subjects with normal hepatic function (n = 10). The pharmacokinetics of unbound paricalcitol was similar across the range of hepatic function evaluated in this study. No dose adjustment is required in patients with mild and moderate hepatic impairment. The influence of severe hepatic impairment on the pharmacokinetics of paricalcitol has not been evaluated.

Renal Impairment

Following administration of ZEMPLAR capsules, the pharmacokinetic profile of paricalcitol for CKD Stage 5 on HD or PD was comparable to that in CKD 3 or 4 patients. Therefore, no special dose adjustments are required other than those recommended in the Dosage and Administration section [see Dosage and Administration (2)].

Drug Interactions

An in vitro study indicates that paricalcitol is neither an inhibitor of CYP1A2, CYP2A6, CYP2B6, CYP2C8, CYP2C9, CYP2C19, CYP2D6, CYP2E1 or CYP3A nor an inducer of CYP2B6, CYP2C9 or CYP3A. Hence, paricalcitol is neither expected to inhibit nor induce the clearance of drugs metabolized by these enzymes.

Omeprazole

The effect of omeprazole (40 mg capsule), a strong inhibitor of CYP2C19, on paricalcitol (four 4 mcg capsules) pharmacokinetics was investigated in a single dose, crossover study in healthy subjects. The pharmacokinetics of paricalcitol was not affected when omeprazole was administered approximately 2 hours prior to the paricalcitol dose.

Ketoconazole

The effect of multiple doses of ketoconazole, a strong inhibitor of CYP3A, administered as 200 mg BID for 5 days on the pharmacokinetics of paricalcitol (4 mcg capsule) has been studied in healthy subjects. The Cmax of paricalcitol was minimally affected, but AUC0-∞ approximately doubled in the presence of ketoconazole. The mean half-life of paricalcitol was 17.0 hours in the presence of ketoconazole as compared to 9.8 hours, when paricalcitol was administered alone [see Drug Interactions (7)].

13 NONCLINICAL TOXICOLOGY

13.1 Carcinogenesis, Mutagenesis and Impairment of Fertility

In a 104-week carcinogenicity study in CD-1 mice, an increased incidence of uterine leiomyoma and leiomyosarcoma was observed at subcutaneous doses of 1, 3, 10 mcg/kg given three times weekly (2 to 15 times the AUC at a human dose of 14 mcg, equivalent to 0.24 mcg/kg based on AUC). The incidence rate of uterine leiomyoma was significantly different than the control group at the highest dose of 10 mcg/kg. In a 104-week carcinogenicity study in rats, there was an increased incidence of benign adrenal pheochromocytoma at subcutaneous doses of 0.15, 0.5, 1.5 mcg/kg (< 1 to 7 times the exposure following a human dose of 14 mcg, equivalent to 0.24 mcg/kg based on AUC). The increased incidence of pheochromocytomas in rats may be related to the alteration of calcium homeostasis by paricalcitol. Paricalcitol did not exhibit genetic toxicity in vitro with or without metabolic activation in the microbial mutagenesis assay (Ames Assay), mouse lymphoma mutagenesis assay (L5178Y), or a human lymphocyte cell chromosomal aberration assay. There was also no evidence of genetic toxicity in an in vivo mouse micronucleus assay. Paricalcitol had no effect on fertility (male or female) in rats at intravenous doses up to 20 mcg/kg/dose (equivalent to 13 times a human dose of 14 mcg based on surface area, mcg/m^2).

14 CLINICAL STUDIES

14.1 Chronic Kidney Disease Stages 3 and 4

Adults

The safety and efficacy of ZEMPLAR capsules were evaluated in three, 24-week, double blind, placebo-controlled, randomized, multicenter, Phase 3 clinical studies in CKD Stages 3 and 4 patients. Two studies used an identical three times a week dosing design, and one study used a daily dosing design. A total of 107 patients received ZEMPLAR capsules and 113 patients received placebo. The mean age of the patients was 63 years, 68% were male, 71% were Caucasian, and 26% were African-American. The average baseline iPTH was 274 pg/mL (range: 145-856 pg/mL). The average duration of CKD prior to study entry was 5.7 years. At study entry 22% were receiving calcium based phosphate binders and/or calcium supplements. Baseline 25-hydroxyvitamin D levels were not measured.

The initial dose of ZEMPLAR capsules was based on baseline iPTH. If iPTH was ≤ 500 pg/mL, ZEMPLAR capsules were administered 1 mcg daily or 2 mcg three times a week, not more than every other day. If iPTH was > 500 pg/mL, ZEMPLAR capsules were administered 2 mcg daily or 4 mcg three times a week, not more than every other day. The dose was increased by 1 mcg daily or 2 mcg three times a week every 2 to 4 weeks until iPTH levels were reduced by at least 30% from baseline. The overall average weekly dose of ZEMPLAR capsules was 9.6 mcg/week in the daily regimen and 9.5 mcg/week in the three times a week regimen.

In the clinical studies, doses were titrated for any of the following reasons: if iPTH fell to < 60 pg/mL, or decreased > 60% from baseline, the dose was reduced or temporarily withheld; if iPTH decreased < 30% from baseline and serum calcium was ≤ 10.3 mg/dL and serum phosphorus was ≤ 5.5 mg/dL, the dose was increased; and if iPTH decreased between 30 to 60% from baseline and serum calcium and phosphorus were ≤ 10.3 mg/dL and ≤ 5.5 mg/dL, respectively, the dose was maintained. Additionally, if serum calcium was between 10.4 to 11.0 mg/dL, the dose was reduced irrespective of iPTH, and the dose was withheld if serum calcium was > 11.0 mg/dL. If serum phosphorus was > 5.5 mg/dL, dietary counseling was provided, and phosphate binders could have been initiated or increased. If the elevation persisted, the ZEMPLAR capsules dose was decreased. Seventy-seven percent (77%) of the ZEMPLAR capsules treated patients and 82% of the placebo treated patients completed the 24-week treatment. The primary efficacy endpoint of at least two consecutive ≥ 30% reductions from baseline iPTH was achieved by 91% of ZEMPLAR capsules treated patients and 13% of the placebo treated patients (p < 0.001). The proportion of ZEMPLAR capsules treated patients achieving two consecutive ≥ 30% reductions was similar between the daily and the three times a week regimens (daily: 30/33, 91%; three times a week: 62/68, 91%).

The incidence of hypercalcemia (defined as two consecutive serum calcium values > 10.5 mg/dL), and hyperphosphatemia in ZEMPLAR capsules treated patients was similar to placebo. There were no treatment related adverse events associated with hypercalcemia or hyperphosphatemia in the ZEMPLAR capsules group. No increases in urinary calcium or phosphorous were detected in ZEMPLAR capsules treated patients compared to placebo.

The pattern of change in the mean values for serum iPTH during the studies is shown in Figure 1.

Figure 1. Mean Values for Serum iPTH Over Time in the Three Double-Blind, Placebo-Controlled, Phase 3, CKD Stages 3 and 4 Studies Combined

The mean changes from baseline to final treatment visit in serum iPTH, calcium, phosphorus, and bone-specific alkaline phosphatase are shown in Table 9.

Table 9. Mean Changes from Baseline to Final Treatment Visit in Serum iPTH, Bone Specific Alkaline Phosphatase, Calcium, Phosphorus, and Calcium x Phosphorus Product in Three Combined Double-Blind, Placebo-Controlled, Phase 3, CKD Stages 3 and 4 Studies
 | ZEMPLAR Capsules | Placebo
iPTH (pg/mL) | n = 104 | n = 110
Mean Baseline Value | 266 | 279
Mean Final Treatment Value | 162 | 315
Mean Change from Baseline (SE) | -104 (9.2) | +35 (9.0)
Bone Specific Alkaline Phosphatase (mcg/L) | n = 101 | n = 107
Mean Baseline | 17.1 | 18.8
Mean Final Treatment Value | 9.2 | 17.4
Mean Change from Baseline (SE) | -7.9 (0.76) | -1.4 (0.74)
Calcium (mg/dL) | n = 104 | n = 110
Mean Baseline | 9.3 | 9.4
Mean Final Treatment Value | 9.5 | 9.3
Mean Change from Baseline (SE) | +0.2 (0.04) | -0.1 (0.04)
Phosphorus (mg/dL) | n = 104 | n = 110
Mean Baseline | 4.0 | 4.0
Mean Final Treatment Value | 4.3 | 4.3
Mean Change from Baseline (SE) | +0.3 (0.08) | +0.3 (0.08)

Pediatric patients 10 to 16 years of age

The safety and efficacy of ZEMPLAR capsules were evaluated in a 12-week, double-blind, placebo-controlled, randomized, multicenter study in pediatric patients ages 10 to 16 years with CKD Stages 3 and 4. A total of 18 patients received ZEMPLAR capsules and 18 patients received placebo during the blinded phase of the study. The mean age of the patients was 13.6 years, 69% were male, 86% were Caucasian, and 8% were Asian.

The initial dose of ZEMPLAR capsules was 1 mcg three times a week. Serum iPTH, calcium, and phosphorus levels were monitored every 2-4 weeks with a goal to maintain levels within target ranges: iPTH 35 to 70pg/mL for CKD stage 3, iPTH 70 to 110pg/mL for CKD stage 4, calcium < 10.2mg/dL, phosphorous < 5.8mg/dL. Starting at Treatment Week 4 and every 4 weeks thereafter, doses may have been increased in 1 mcg increments three times a week (e.g., increase from 1 mcg three times per week to 2 mcg three times per week) based upon safety observations and blood chemistry evaluations. Each administered dose could be decreased in 1 mcg increments three times a week, or held if the patient was receiving a 1 mcg dose, as appropriate at any time. The average cumulative weekly dose of ZEMPLAR was 4mcg/week during the 12 week blinded treatment period.

The primary efficacy endpoint, the proportion of Stage 3 and 4 patients achieving two consecutive ≥ 30% reductions from baseline in iPTH levels, was statistically significant during the 12-week blinded phase. Results are shown in Table 10.

Table 10. Changes in iPTH from Baseline in the CKD Stages 3 and 4 Pediatric Study
Phase/Treatment | Two Consecutive ≥ 30% Reductions From Baseline in iPTH Levelsa
Blinded Phase
Placebo | 0/18 (0%)
ZEMPLAR | 5/18 (28%)*
* p < 0.05 compared to placebo
a. The analysis treats 3 patients on ZEMPLAR and 1 patient on placebo with unknown response status as non-responders.

14.2 Chronic Kidney Disease Stage 5

Adults

The safety and efficacy of ZEMPLAR capsules were evaluated in a Phase 3, 12-week, double blind, placebo-controlled, randomized, multicenter study in patients with CKD Stage 5 on HD or PD. The study used a three times a week dosing design. A total of 61 patients received ZEMPLAR capsules and 27 patients received placebo. The mean age of the patients was 57 years, 67% were male, 50% were Caucasian, 45% were African- American, and 53% were diabetic. The average baseline serum iPTH was 701 pg/mL (range: 216-1933 pg/mL). The average time since first dialysis across all subjects was 3.3 years.

The initial dose of ZEMPLAR capsules was based on baseline iPTH/60. Subsequent dose adjustments were based on iPTH/60 as well as primary chemistry results that were measured once a week. Starting at Treatment Week 2, study drug was maintained, increased or decreased weekly based on the results of the previous week’s calculation of iPTH/60. ZEMPLAR capsules were administered three times a week, not more than every other day.

The proportion of patients achieving at least two consecutive weekly ≥ 30% reductions from baseline serum iPTH was 88% of ZEMPLAR capsules treated patients and 13% of the placebo treated patients. The proportion of patients achieving at least two consecutive weekly ≥ 30% reductions from baseline iPTH was similar for HD and PD patients.

The incidence of hypercalcemia (defined as two consecutive serum calcium values > 10.5 mg/dL) in patients treated with ZEMPLAR capsules was 6.6% as compared to 0% for patients given placebo. In PD patients the incidence of hypercalcemia in patients treated with ZEMPLAR capsules was 21% as compared to 0% for patients given placebo. The patterns of change in the mean values for serum iPTH are shown in Figure 2. The rate of hypercalcemia with ZEMPLAR capsules may be reduced with a lower dosing regimen based on the iPTH/80 formula as shown by computer simulations. The hypercalcemia rate can be further predicted to decrease, if the treatment is initiated in only those with baseline serum calcium ≤ 9.5 mg/dL [see Clinical Pharmacology (12.2) and Dosage and Administration (2.2)].

Figure 2. Mean Values for Serum iPTH Over Time in a Phase 3, Double-Blind, Placebo-Controlled CKD Stage 5 Study

16 HOW SUPPLIED/STORAGE AND HANDLING

ZEMPLAR capsules are available as 1 mcg and 2 mcg capsules.

The 1 mcg capsule is an oval, gray, soft gelatin capsule supplied and imprinted as follows:

Bottles of 30 – NDC 0074-9036-30 (imprinted with “ZA”)

Bottles of 30 – NDC 0074-4317-30 (imprinted with the “a” logo and “ZA”)

The 2 mcg capsule is an oval, orange-brown, soft gelatin capsule supplied and imprinted as follows:

Bottles of 30 – NDC 0074-9037-30 (imprinted with “ZF”)

Bottles of 30 – NDC 0074-4314-30 (imprinted with the “a” logo and “ZF”)

Storage

Store ZEMPLAR capsules at 25°C (77°F). Excursions permitted between 15°- 30°C (59°- 86°F). See USP Controlled Room Temperature.

17 PATIENT COUNSELING INFORMATION

Advise patients of the following:

- The most common adverse reactions with use of ZEMPLAR capsules include diarrhea, hypertension, nausea, nasopharyngitis, dizziness, and vomiting.
- Patients should adhere to instructions regarding diet and phosphorus restriction.
- Patients should contact a health care provider if they develop symptoms of elevated calcium, (e.g. feeling tired, difficulty thinking clearly, loss of appetite, nausea, vomiting, constipation, increased thirst, increased urination and weight loss).
- Patients should return to the physician's office for routine monitoring. More frequent monitoring is necessary during the initiation of therapy, following dose changes or when potentially interacting medications are started or discontinued.
- Patients should inform their physician of all medications, including prescription and nonprescription drugs, supplements, and herbal preparations they are taking and any change to their medical condition. Patients should also inform their physician that they are taking ZEMPLAR capsules if a new medication is prescribed.
- Breastfeeding is not recommended during treatment with ZEMPLAR capsules [see Use in Specific Populations (8.2)].

© 2024 AbbVie. All rights reserved.

ZEMPLAR and its design are trademarks of AbbVie Inc.

Manufactured for

AbbVie Inc.

North Chicago, IL 60064, U.S.A.

131899 R1 August 2024

PACKAGE LABEL

NDC 0074–9036–30

Zemplar® (paricalcitol) Capsules

1 mcg 30 Capsules

Rx only abbvie

PACKAGE LABEL

NDC 0074–9037–30

Zemplar® (paricalcitol) Capsules

2 mcg 30 Capsules

Rx only abbvie

PACKAGE LABEL

NDC 0074–4317–30

Zemplar® (paricalcitol) Capsules

1 mcg 30 Capsules

Rx only abbvie

PACKAGE LABEL

NDC 0074–4314–30

Zemplar® (paricalcitol) Capsules

2 mcg 30 Capsules

Rx only abbvie